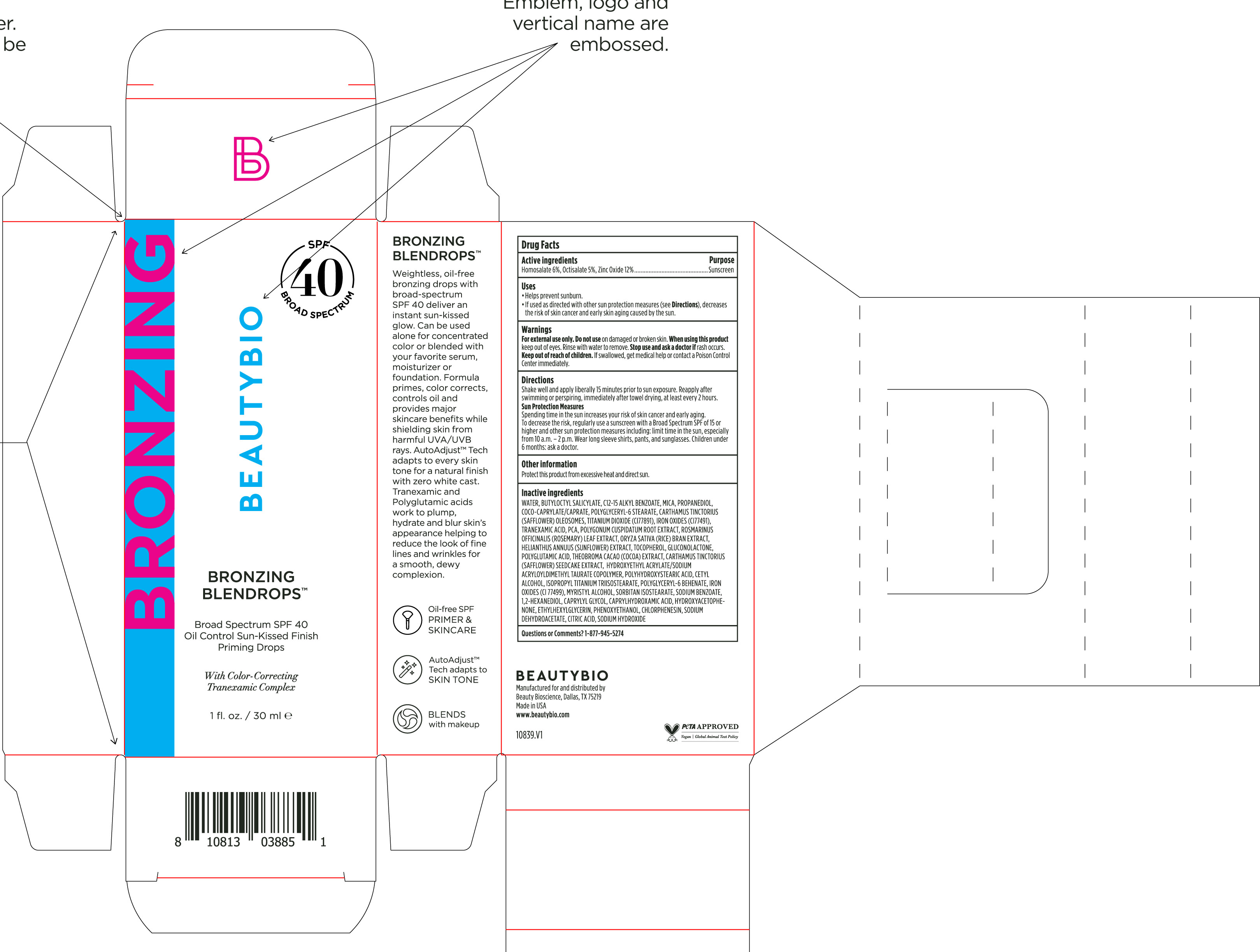 DRUG LABEL: Bronzing Blendrops Broad Spectrum SPF 40
NDC: 44717-082 | Form: SOLUTION/ DROPS
Manufacturer: Wasatch Product Development, LLC
Category: otc | Type: HUMAN OTC DRUG LABEL
Date: 20251209

ACTIVE INGREDIENTS: HOMOSALATE 6 g/100 mL; OCTISALATE 5 g/100 mL; ZINC OXIDE 12 g/100 mL
INACTIVE INGREDIENTS: HELIANTHUS ANNUUS FLOWERING TOP; TOCOPHEROL; MICA; 1,2-HEXANEDIOL; SODIUM DEHYDROACETATE; POLYGLYCERYL-6 BEHENATE; FERROSOFERRIC OXIDE; CAPRYLHYDROXAMIC ACID; CAPRYLYL GLYCOL; ROSEMARY; RICE BRAN; GLUCONOLACTONE; CITRIC ACID MONOHYDRATE; ETHYLHEXYLGLYCERIN; COCOYL CAPRYLOCAPRATE; POLYGLYCERYL-6 STEARATE; TRANEXAMIC ACID; CETYL ALCOHOL; ALKYL (C12-15) BENZOATE; COCOA; POLYHYDROXYSTEARIC ACID (2300 MW); ISOPROPYL TITANIUM TRIISOSTEARATE; PHENOXYETHANOL; CHLORPHENESIN; BUTYLOCTYL SALICYLATE; REYNOUTRIA JAPONICA ROOT; HYDROXYACETOPHENONE; CARTHAMUS TINCTORIUS SEEDCAKE; SODIUM HYDROXIDE; WATER; CARTHAMUS TINCTORIUS SEED OLEOSOMES; TITANIUM DIOXIDE; FERRIC OXIDE RED; PROPANEDIOL; PIDOLIC ACID; SORBITAN ISOSTEARATE; HYDROXYETHYL ACRYLATE/SODIUM ACRYLOYLDIMETHYL TAURATE COPOLYMER (45000 MPA.S AT 1%); MYRISTYL ALCOHOL; SODIUM BENZOATE

Bronzing Blendrops Broad Spectrum SPF 40

Active Ingredients
Homosalate 6%

Octisalate 5%

Zinc Oxide 12 %

Purpose

Sunscreen

Uses

· helps prevent sunburn
· If used as directed with other sun protection measures (see Directions), decreases the risk of skin cancer and early skin aging caused by the sun

Keep out of reach of children. If swallowed, get medical help or contact a Poison Control Center right away.

- Stop use and ask a doctor if rash occurs.

Warnings

For external use only. Do not use on damaged or broken skin. When using this product keep out of eyes. Rinse with water to remove.

Directions
Shake well and apply liberally 15 minutes before sun exposure. Reapply after swimming or perspiring, immediately after towel drying, at least every 2 hours.
Sun Protection Measures

Spending time in the sun increases your risk of skin cancer and early skin aging. To decrease this risk, regularly use a sunscreen
with broad spectrum SPF of 15 or higher and other sun protection measures including: limit time in the sun, especially from 10 a.m. - 2 p.m. Wear long-sleeve shirts, pants, hats, and sunglasse. Children under 6 months: Ask a doctor

Other information

Protect this product from excessive heat and direct sun

INACTIVE INGREDIENT

Water, Butyloctyl Salicylate, C12-15 Alkyl Benozate, Mica, Propanediol, Coco-Caprylate/Caprate, Polyglyceryl-6 Stearate, Carthamus Tinctorius (Safflower) Oleosomes, Titanium Dioxide (CI77891), Iron Oxides (CI 77491), Tranexamic Acid, PCA, Polygonum Cuspidatum Root Extract, Rosmarinus Officinalis (Rosemary) Leaf Extract, Oryza Sativa (Rice) Bran Extract, Helianthus Annuus (Sunflower) Extract, Tocopherol, Gluconolactone, Polyglutamic Acid, Theobroma Cacao (Cocoa) Extract, Carthamus Tinctorius (Safflower) Seedcake Extract, Hydroxyethyl Acrylate/Sodium Acryloyldimethyl Taurate Copolymer, Polyhydroxystearic Acid, Cetyl Alcohol, Isopropyl Titanium Triisostearate, Polyglyceryl-6 Behenate, Iron Oxides (CI 77499), Myristyl Alcohol, Sorbitan Isostearate, Sodium Benzoate, 1,2-Hexanediol, Caprylyl Glycol, Caprylhydroxamic Acid, Hydroxyacetophenone, Ethylhexylglycerin, Phenoxyethanol, Chlorphenesin, Sodium Dehydroacetate, Citric Acid, Sodium Hydroxide

Questions or Comments? 1-877-945-5274

PACKAGE LABEL

Bronzing Blendrops

Broad Spectrum SPF 40

Oil Control Sun-kissed Finish Priming Drops

1 fl. oz. / 30 ml